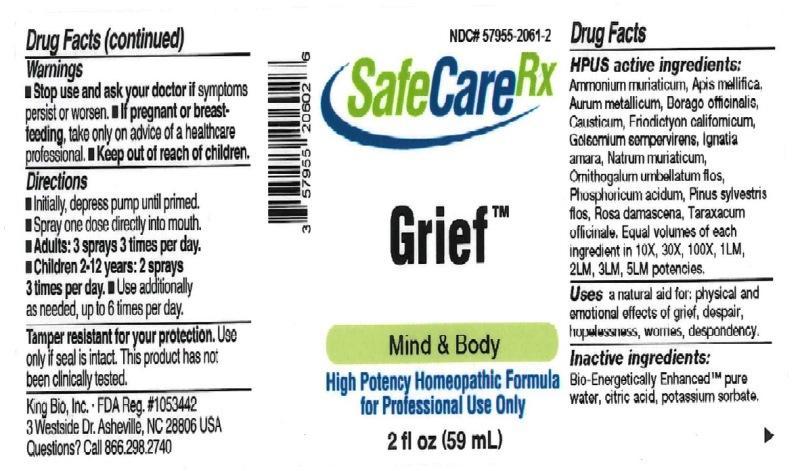 DRUG LABEL: Grief
NDC: 57955-2061 | Form: LIQUID
Manufacturer: King Bio Inc.
Category: homeopathic | Type: HUMAN OTC DRUG LABEL
Date: 20161110

ACTIVE INGREDIENTS: AMMONIUM CHLORIDE 10 [hp_X]/59 mL; APIS MELLIFERA 10 [hp_X]/59 mL; GOLD 10 [hp_X]/59 mL; BORAGE 10 [hp_X]/59 mL; CAUSTICUM 10 [hp_X]/59 mL; ERIODICTYON CALIFORNICUM LEAF 10 [hp_X]/59 mL; GELSEMIUM SEMPERVIRENS ROOT 10 [hp_X]/59 mL; STRYCHNOS IGNATII SEED 10 [hp_X]/59 mL; SODIUM CHLORIDE 10 [hp_X]/59 mL; ORNITHOGALUM UMBELLATUM FLOWERING TOP 10 [hp_X]/59 mL; PHOSPHORIC ACID 10 [hp_X]/59 mL; PINUS SYLVESTRIS FLOWERING TOP 10 [hp_X]/59 mL; ROSA DAMASCENA FLOWERING TOP 10 [hp_X]/59 mL; TARAXACUM OFFICINALE 10 [hp_X]/59 mL
INACTIVE INGREDIENTS: WATER; ANHYDROUS CITRIC ACID; POTASSIUM SORBATE

Grief™

ACTIVE INGREDIENT

Drug Facts__________________________________________________________________________________________________________

HPUS active ingredients: Ammonium muriaticum, Apis mellifica, Aurum metallicum, Borago officinalis, Causticum, Eriodictyon californicum, Gelsemium sempervirens, Ignatia amara, Natrum muriaticum, Ornithogalum umbellatum, flos, Phosphoricum acidum, Pinus sylvestris, flos, Rosa damascena, Taraxacum officinale. Equal volumes of each ingredient in 10X, 30X, 100X, 1LM, 2LM, 3LM, 5LM potencies.

INDICATIONS AND USAGE

Uses a natural aid for: physical and emotional effects of grief, despair, hopelessness, worries, despondency.

INACTIVE INGREDIENT

Inactive Ingredients: Bio-Energetically Enhanced™ pure water, citric acid and potassium sorbate.

Warnings

- Stop use and ask your doctor if symptoms persist or worsen.
- If pregnant or breast-feeding, take only on advice of a healthcare professional.

- Keep out of reach of children.

DOSAGE AND ADMINISTRATION

- Directions Initially, depress pump until primed.
- Spray one dose directly into mouth.
- Adults: 3 sprays 3 times per day.
- Children 2 - 12: 2 sprays 3 times per day.
- Use additionally as needed, up to 6 times per day.

OTHER SAFETY INFORMATION

Tamper resistant for your protection. Use only if safety seal is intact. This product has not been clinically tested.

PURPOSE

Uses a natural aid for:

- physical and emotional effects of grief
- despair
- hopelessness
- worries
- despondency